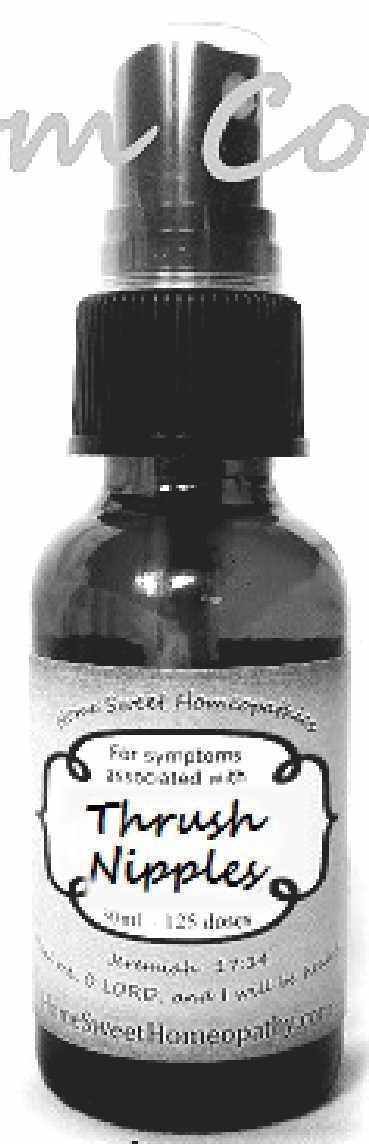 DRUG LABEL: Thrush Nipples
NDC: 59667-0002 | Form: SPRAY
Manufacturer: Home Sweet Homeopathics
Category: homeopathic | Type: HUMAN OTC DRUG LABEL
Date: 20130808

ACTIVE INGREDIENTS: BAPTISIA TINCTORIA ROOT 30 [hp_C]/30 [hp_C]; BRYONIA ALBA ROOT 30 [hp_C]/30 [hp_C]; SODIUM BORATE 30 [hp_C]/30 [hp_C]; CANDIDA ALBICANS 30 [hp_C]/30 [hp_C]; CALENDULA OFFICINALIS FLOWERING TOP 30 [hp_C]/30 [hp_C]; GOLDENSEAL 30 [hp_C]/30 [hp_C]; POTASSIUM CHLORATE 30 [hp_C]/30 [hp_C]; MERCURIUS SOLUBILIS 30 [hp_C]/30 [hp_C]; SODIUM CHLORIDE 30 [hp_C]/30 [hp_C]; NUTMEG 30 [hp_C]/30 [hp_C]; STRYCHNOS NUX-VOMICA SEED 30 [hp_C]/30 [hp_C]; PHOSPHORUS 30 [hp_C]/30 [hp_C]; SUCROSE 30 [hp_C]/30 [hp_C]; SULFURIC ACID 30 [hp_C]/30 [hp_C]; DELPHINIUM STAPHISAGRIA SEED 30 [hp_C]/30 [hp_C]
INACTIVE INGREDIENTS: WATER; ALCOHOL

PURPOSE

For symptoms associated with

To be used according to label indications.

Active Ingredients:

Baptisia, Bryonia, Borax, Candida A, Calendula, Hydrastis, Kali Chloricum, Mercurius Sol, Nat Mur, Nux Moschata, Nux Vomica, Phosphorus, Saccharum Album, Sulphuricum Acidum, Staphysagria,

Directions:

Spritz 1 time under the tongue 3 x per day until improvement is seen, then dose 1x per day for 3 days. Dose when symptoms return.

Keep out of reach of children.

WARNINGS

If no improvement is seen after 7 days or new symptoms develop, discontinue use.

Inactive Ingredients:

In reverse osmosis water with less than 1% alcohol. May contain trace amounts of lactose.